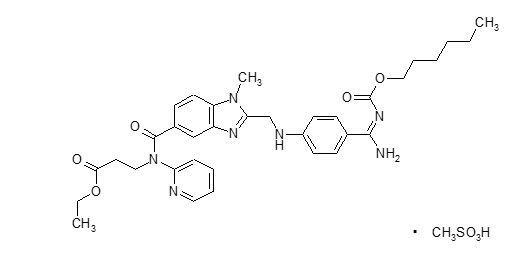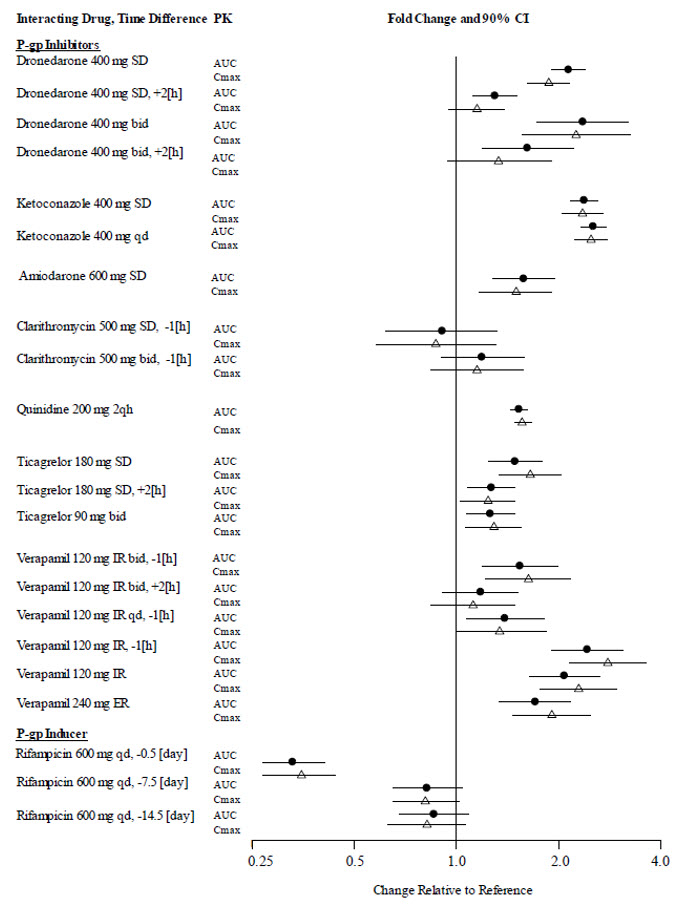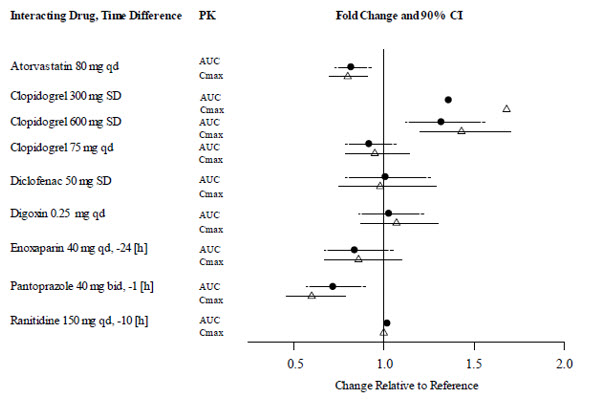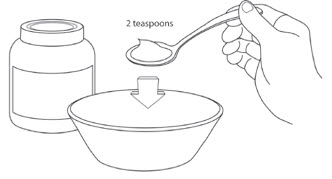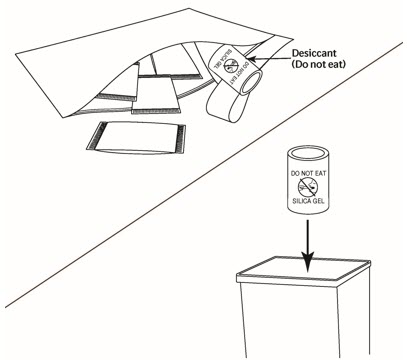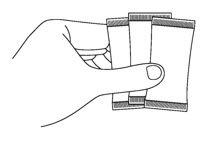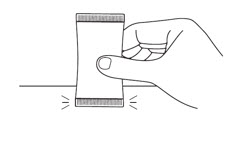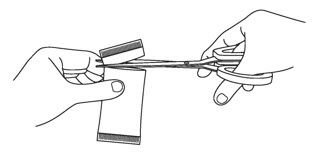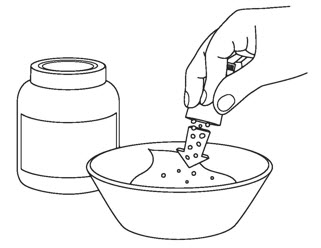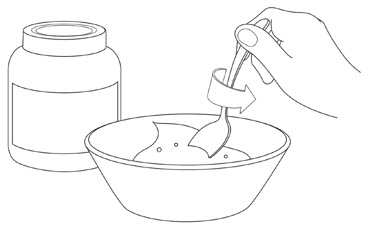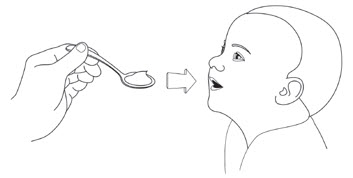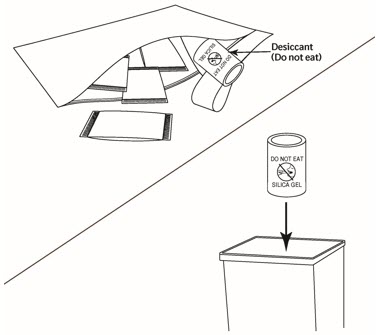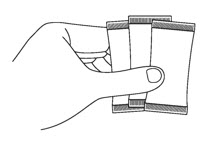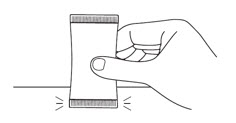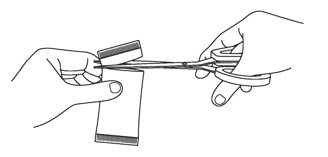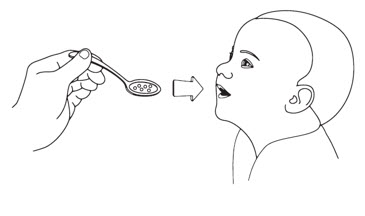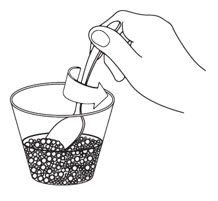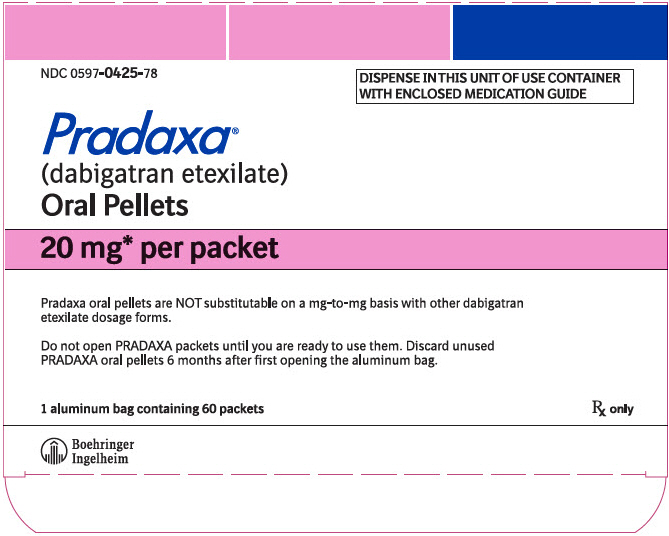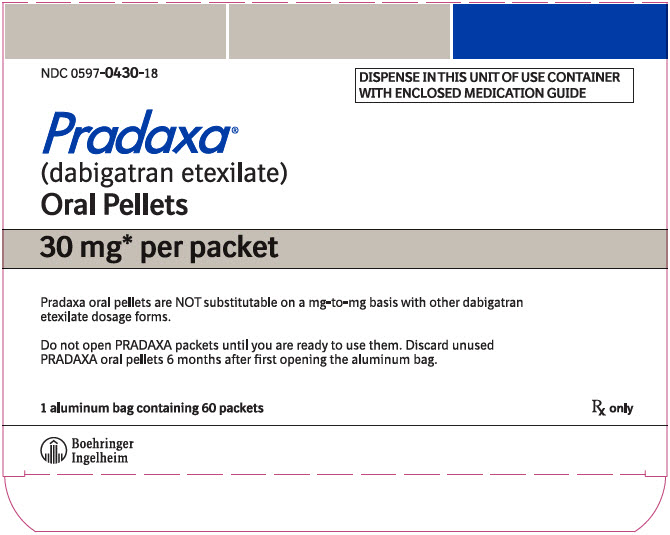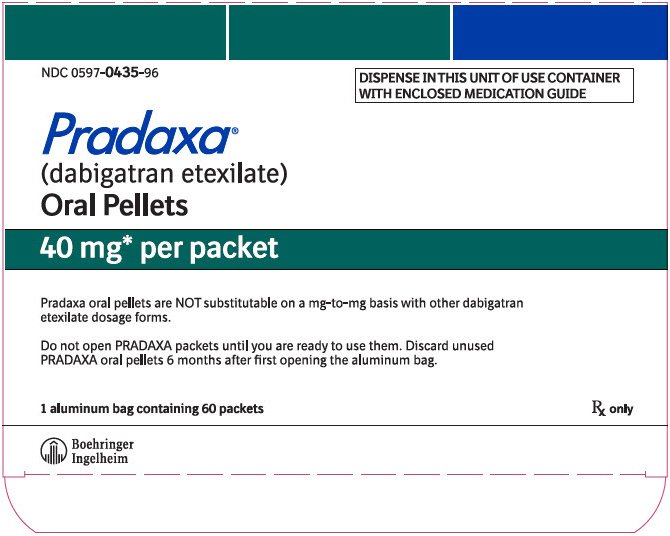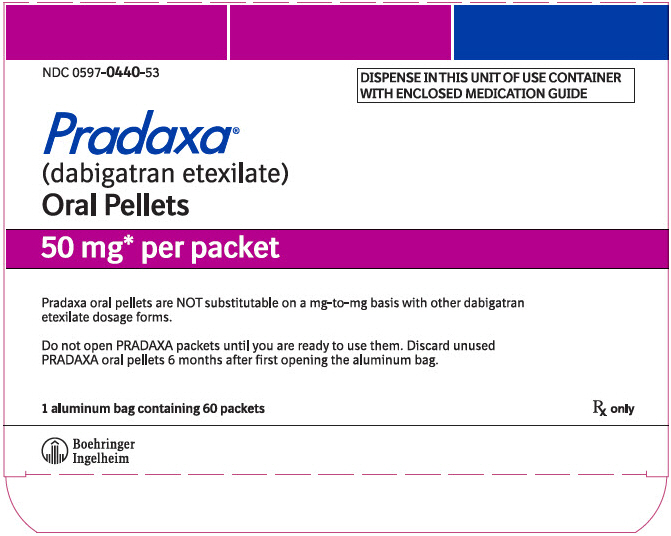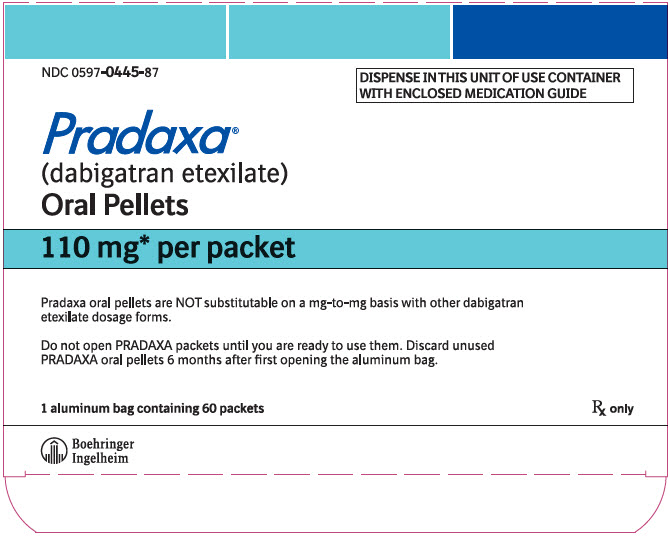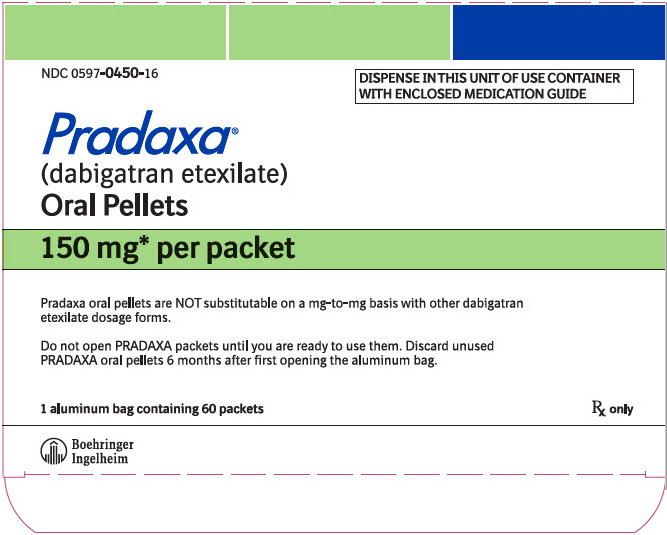 DRUG LABEL: Pradaxa
NDC: 0597-0425 | Form: PELLET
Manufacturer: Boehringer Ingelheim Pharmaceuticals, Inc.
Category: prescription | Type: HUMAN PRESCRIPTION DRUG LABEL
Date: 20250627

ACTIVE INGREDIENTS: DABIGATRAN ETEXILATE MESYLATE 20 mg/1 1
INACTIVE INGREDIENTS: ACACIA; DIMETHICONE; HYPROMELLOSE, UNSPECIFIED; HYDROXYPROPYL CELLULOSE (1600000 WAMW); TALC; TARTARIC ACID

HIGHLIGHTS OF PRESCRIBING INFORMATION

These highlights do not include all the information needed to use PRADAXA Oral Pellets safely and effectively. See full prescribing information for PRADAXA Oral Pellets.
PRADAXA® (dabigatran etexilate) oral pellets
Initial U.S. Approval: 2010

WARNING: (A) PREMATURE DISCONTINUATION OF PRADAXA INCREASES THE RISK OF THROMBOTIC EVENTS, and (B) SPINAL/EPIDURAL HEMATOMA

See full prescribing information for complete boxed warning

(A) PREMATURE DISCONTINUATION OF PRADAXA INCREASES THE RISK OF THROMBOTIC EVENTS: Premature discontinuation of any oral anticoagulant, including PRADAXA, increases the risk of thrombotic events. To reduce this risk, consider coverage with another anticoagulant if PRADAXA is discontinued for a reason other than pathological bleeding or completion of a course of therapy (2.5, 2.6, 2.7, 5.1).

(B) SPINAL/EPIDURAL HEMATOMA: Epidural or spinal hematomas may occur in patients treated with PRADAXA who are receiving neuraxial anesthesia or undergoing spinal puncture. These hematomas may result in long-term or permanent paralysis (5.3). Monitor patients frequently for signs and symptoms of neurological impairment and if observed, treat urgently. Consider the benefits and risks before neuraxial intervention in patients who are or who need to be anticoagulated (5.3).

1 INDICATIONS AND USAGE

PRADAXA Oral Pellets are a direct thrombin inhibitor indicated:

- For the treatment of venous thromboembolic events (VTE) in pediatric patients aged 3 months to less than 12 years of age who have been treated with a parenteral anticoagulant for at least 5 days (1.1)
- To reduce the risk of recurrence of VTE in pediatric patients aged 3 months to less than 12 years of age who have been previously treated (1.2)

2 DOSAGE AND ADMINISTRATION

- Treatment of Pediatric Venous Thromboembolic Events (VTE):
  - For pediatric patients aged 3 months to less than 2 years: age- and weight-based dosage, twice daily after at least 5 days of parenteral anticoagulant (2.2)
  - For pediatric patients 2 years to less than 12 years: weight-based dosage, twice daily after at least 5 days of parenteral anticoagulant (2.2)
- Reduction in the Risk of Recurrence of Pediatric VTE:
  - For pediatric patients aged 3 months to less than 2 years: age- and weight-based dosage, twice daily after previous treatment (2.2)
  - For pediatric patients aged 2 years to less than 12 years: weight-based dosage, twice daily after previous treatment (2.2)
- Pradaxa Oral Pellets are NOT substitutable on a milligram-to-milligram basis with other dabigatran etexilate dosage forms (2.1)
- Review recommendations for converting to or from other oral or parenteral anticoagulants (2.5, 2.6)
- Temporarily discontinue PRADAXA before invasive or surgical procedures when possible, then restart promptly (2.7)

3 DOSAGE FORMS AND STRENGTHS

Oral pellets: 20 mg, 30 mg, 40 mg, 50 mg, 110 mg, 150 mg per packet (3)

4 CONTRAINDICATIONS

- Active pathological bleeding (4)
- History of serious hypersensitivity reaction to PRADAXA (4)
- Mechanical prosthetic heart valve (4)

5 WARNINGS AND PRECAUTIONS

- Bleeding: PRADAXA can cause serious and fatal bleeding (5.2)
- Bioprosthetic heart valves: PRADAXA use not recommended (5.4)
- Increased Risk of Thrombosis in Patients with Triple-Positive Antiphospholipid Syndrome: PRADAXA use not recommended (5.6)

6 ADVERSE REACTIONS

Most common adverse reactions (> 15%) are gastrointestinal adverse reactions and bleeding. (6.1)

To report SUSPECTED ADVERSE REACTIONS, contact Boehringer Ingelheim Pharmaceuticals, Inc. at (800) 542-6257 or FDA at 1-800-FDA-1088 or www.fda.gov/medwatch.

7 DRUG INTERACTIONS

- P-gp inducers: Avoid coadministration with PRADAXA (5.5)
- The concomitant use of PRADAXA with P-gp inhibitors has not been studied in pediatric patients but may increase exposure to dabigatran (5.5, 7)

8 USE IN SPECIFIC POPULATIONS

- Lactation: Breastfeeding not recommended (8.2)

FULL PRESCRIBING INFORMATION

WARNING: (A) PREMATURE DISCONTINUATION OF PRADAXA INCREASES THE RISK OF THROMBOTIC EVENTS, and (B) SPINAL/EPIDURAL HEMATOMA

(A) PREMATURE DISCONTINUATION OF PRADAXA INCREASES THE RISK OF THROMBOTIC EVENTS

Premature discontinuation of any oral anticoagulant, including PRADAXA, increases the risk of thrombotic events. If anticoagulation with PRADAXA is discontinued for a reason other than pathological bleeding or completion of a course of therapy, consider coverage with another anticoagulant [see Dosage and Administration (2.5, 2.6, 2.7) and Warnings and Precautions (5.1)].

(B) SPINAL/EPIDURAL HEMATOMA

Epidural or spinal hematomas may occur in patients treated with PRADAXA who are receiving neuraxial anesthesia or undergoing spinal puncture. These hematomas may result in long-term or permanent paralysis. Consider these risks when scheduling patients for spinal procedures. Factors that can increase the risk of developing epidural or spinal hematomas in these patients include:

- use of indwelling epidural catheters
- concomitant use of other drugs that affect hemostasis, such as non-steroidal anti-inflammatory drugs (NSAIDs), platelet inhibitors, other anticoagulants
- a history of traumatic or repeated epidural or spinal punctures
- a history of spinal deformity or spinal surgery
- optimal timing between the administration of PRADAXA and neuraxial procedures is not known [see Warnings and Precautions (5.3)].

Monitor patients frequently for signs and symptoms of neurological impairment. If neurological compromise is noted, urgent treatment is necessary [see Warnings and Precautions (5.3)].

Consider the benefits and risks before neuraxial intervention in patients anticoagulated or to be anticoagulated [see Warnings and Precautions (5.3)].

1 INDICATIONS AND USAGE

1.1 Treatment of Venous Thromboembolic Events in Pediatric Patients

PRADAXA Oral Pellets are indicated for the treatment of venous thromboembolic events (VTE) in pediatric patients aged 3 months to less than 12 years of age who have been treated with a parenteral anticoagulant for at least 5 days.

1.2 Reduction in the Risk of Recurrence of Venous Thromboembolic Events in Pediatric Patients

PRADAXA Oral Pellets are indicated to reduce the risk of recurrence of VTE in pediatric patients aged 3 months to less than 12 years of age who have been previously treated.

2 DOSAGE AND ADMINISTRATION

2.1 Important Dosage Information

Dabigatran etexilate is available in different dosage forms and not all dosage forms are approved for the same indications and age groups. In addition, there are differences between the dosage forms with respect to dosing due to differences in bioavailability. Do not substitute different dosage forms (for example, capsules) for oral pellets on a milligram-to-milligram basis and do not combine more than one dosage form to achieve the total dose [see Clinical Pharmacology (12.3)].

2.2 Recommended PRADAXA Oral Pellets Dosage for Pediatric Patients

PRADAXA Oral Pellets can be used in pediatric patients aged 3 months to less than 12 years as soon as they are able to swallow soft food. For the treatment of VTE in pediatric patients, treatment should be initiated following treatment with a parenteral anticoagulant for at least 5 days. For reduction in risk of recurrence of VTE, treatment should be initiated following previous treatment.

The recommended dosage of PRADAXA Oral Pellets is based on the patient's age and actual weight as shown in the tables below. PRADAXA Oral Pellets is administered twice daily. Adjust the dosage according to age and actual weight as treatment progresses.

Table 1 Age- and Weight-Based Dosage for PRADAXA Oral Pellets for Pediatric Patients less than 2 Years Old
Actual Weight (kg) | Age (in months) | Dosage (mg) twice daily | Number of Packets Needed
3 kg to less than 4 kg | 3 to less than 6 months | 30 mg | one 30 mg packet twice daily
4 kg to less than 5 kg | 3 to less than 10 months | 40 mg | one 40 mg packet twice daily
5 kg to less than 7 kg | 3 to less than 5 months | 40 mg | one 40 mg packet twice daily
5 kg to less than 7 kg | 5 to less than 24 months | 50 mg | one 50 mg packet twice daily
7 kg to less than 9 kg | 3 to less than 4 months | 50 mg | one 50 mg packet twice daily
7 kg to less than 9 kg | 4 to less than 9 months | 60 mg | two 30 mg packets twice daily
7 kg to less than 9 kg | 9 to less than 24 months | 70 mg | one 30 mg packet plus one 40 mg packet twice daily
9 kg to less than 11 kg | 5 to less than 6 months | 60 mg | two 30 mg packets twice daily
9 kg to less than 11 kg | 6 to less than 11 months | 80 mg | two 40 mg packets twice daily
9 kg to less than 11 kg | 11 to less than 24 months | 90 mg | one 40 mg packet plus one 50 mg packet twice daily
11 kg to less than 13 kg | 8 to less than 18 months | 100 mg | two 50 mg packets twice daily
11 kg to less than 13 kg | 18 to less than 24 months | 110 mg | one 110 mg packet twice daily
13 kg to less than 16 kg | 10 to less than 11 months | 100 mg | two 50 mg packets twice daily
13 kg to less than 16 kg | 11 to less than 24 months | 140 mg | one 30 mg packet plus one 110 mg packet twice daily
16 kg to less than 21 kg | 12 to less than 24 months | 140 mg | one 30 mg packet plus one 110 mg packet twice daily
21 kg to less than 26 kg | 18 to less than 24 months | 180 mg | one 30 mg packet plus one 150 mg packet twice daily

Table 2 Weight-Based Dosage for PRADAXA Oral Pellets for Pediatric Patients between 2 Years to less than 12 Years Old
Actual Weight (kg) | Dosage (mg) twice daily | Number of Packets Needed
7 kg to less than 9 kg | 70 mg | one 30 mg packet plus one 40 mg packet twice daily
9 kg to less than 11 kg | 90 mg | one 40 mg packet plus one 50 mg packet twice daily
11 kg to less than 13 kg | 110 mg | one 110 mg packet twice daily
13 kg to less than 16 kg | 140 mg | one 30 mg packet plus one 110 mg packet twice daily
16 kg to less than 21 kg | 170 mg | one 20 mg packet plus one 150 mg packet twice daily
21 kg to less than 41 kg | 220 mg | two 110 mg packets twice daily
41 kg or greater | 260 mg | one 110 mg packet plus one 150 mg packet twice daily

Evaluation of the extent of anticoagulation in pediatric patients on PRADAXA Oral Pellets may be accomplished using dTT or ECT, and not INR [see Warnings and Precautions (5.2) and Clinical Pharmacology (12.2)].

2.3 Dosage Adjustments

Pediatric Patients with Renal Impairment

Assess renal function prior to initiation of treatment with PRADAXA Oral Pellets. Periodically assess renal function as clinically indicated (i.e., more frequently in clinical situations that may be associated with a decline in renal function) and adjust therapy accordingly. Discontinue PRADAXA Oral Pellets in patients who develop acute renal failure while on PRADAXA Oral Pellets and consider alternative anticoagulant therapy.

Prior to the initiation of treatment with PRADAXA Oral Pellets, estimate the glomerular filtration rate (eGFR) using the Schwartz formula, eGFR (Schwartz) = (0.413 × height in cm) / serum creatinine in mg/dL.

Due to lack of data in pediatric patients with an eGFR < 50 mL/min/1.73 m^2 and the risk of increased exposure, avoid use of PRADAXA Oral Pellets in these patients. Treat patients with an eGFR > 50 mL/min/1.73 m^2 with the dosage according to Tables 1 and 2 [see Dosage and Administration (2.2)].

2.4 Administration

PRADAXA Oral Pellets are administered twice daily, one dose in the morning and one dose in the evening, at approximately the same time every day. The dosing interval should be as close to 12 hours as possible.

If a dose of PRADAXA Oral Pellets is not taken at the scheduled time, the dose should be taken as soon as possible on the same day; the missed dose should be skipped if it cannot be taken at least 6 hours before the next scheduled dose. The dose of PRADAXA Oral Pellets should not be doubled to make up for a missed dose.

If a partial dose has been taken, a second dose should not be administered at that time. The next dose should be taken as scheduled approximately 12 hours later.

The prepared medication should be given before meals to ensure that the patient takes the full dose.

PRADAXA Oral Pellets should be administered immediately after mixing or within 30 minutes after mixing. If the PRADAXA dose is not administered within 30 minutes of mixing, the dose should be discarded, and a new dose prepared.

PRADAXA Oral Pellets should be administered with only specific soft foods or apple juice.

Administration with soft foods

PRADAXA Oral Pellets may be mixed with two teaspoons of the following soft foods at room temperature:

- Mashed carrots
- Apple sauce
- Mashed banana

Administration with apple juice

PRADAXA Oral Pellets may be spooned directly into the patient's mouth and swallowed with apple juice or added to approximately 1-2 ounces of apple juice for drinking.

PRADAXA Oral Pellets should not be administered:

- via syringes or feeding tubes
- with milk, milk products, or soft foods containing milk products

Instruct patients/caregivers to discard the desiccant once the package is opened.

See Instructions for Use.

2.5 Converting from or to Warfarin

When converting patients from warfarin therapy to PRADAXA Oral Pellets, discontinue warfarin and start PRADAXA Oral Pellets when the INR is below 2.0.

When converting from PRADAXA Oral Pellets to warfarin, adjust the starting time of warfarin as follows:

- For eGFR ≥ 50 mL/min/1.73 m^2, start warfarin 3 days before discontinuing PRADAXA Oral Pellets.
- Patients with an eGFR < 50 mL/min/1.73 m^2 have not been studied. Avoid use of PRADAXA Oral Pellets in these patients.

Because PRADAXA Oral Pellets can increase INR, the INR will better reflect warfarin's effect only after PRADAXA Oral Pellets have been stopped for at least 2 days [see Clinical Pharmacology (12.2)].

2.6 Converting from or to Parenteral Anticoagulants

For pediatric patients currently receiving a parenteral anticoagulant, start PRADAXA Oral Pellets 0 to 2 hours before the time that the next dose of the parenteral drug was to have been administered or at the time of discontinuation of a continuously administered parenteral drug (e.g., intravenous unfractionated heparin).

For pediatric patients currently taking PRADAXA Oral Pellets, wait 12 hours after the last dose before switching to a parenteral anticoagulant [see Clinical Pharmacology (12.3)].

2.7 Discontinuation for Surgery and Other Interventions

If possible, discontinue PRADAXA Oral Pellets before invasive or surgical procedures because of the increased risk of bleeding. For pediatric patients, PRADAXA Oral Pellets should be stopped 24 hours before an elective surgery (eGFR > 80 mL/min/1.73 m^2) or 2 days before an elective surgery (eGFR 50-80 mL/min/1.73 m^2). Pediatric patients with an eGFR < 50 mL/min/1.73 m^2 have not been studied, avoid use of PRADAXA Oral Pellets in these patients.

Consider longer times for patients undergoing major surgery, spinal puncture, or placement of a spinal or epidural catheter or port, in whom complete hemostasis may be required [see Use in Specific Populations (8.6) and Clinical Pharmacology (12.3)].

If surgery cannot be delayed, there is an increased risk of bleeding [see Warnings and Precautions (5.2)]. This risk of bleeding should be weighed against the urgency of intervention [see Warnings and Precautions (5.1, 5.3)]. In adults, a specific reversal agent (idarucizumab) is available in case of emergency surgery or urgent procedures when reversal of the anticoagulant effect of dabigatran is needed. Efficacy and safety of idarucizumab have not been established in pediatric patients [see Warnings and Precautions (5.2)]. Refer to the idarucizumab prescribing information for additional information. Restart PRADAXA Oral Pellets as soon as medically appropriate.

3 DOSAGE FORMS AND STRENGTHS

PRADAXA Oral Pellets are available in the following strengths:

- 20 mg yellowish pellets in a packet
- 30 mg yellowish pellets in a packet
- 40 mg yellowish pellets in a packet
- 50 mg yellowish pellets in a packet
- 110 mg yellowish pellets in a packet
- 150 mg yellowish pellets in a packet

4 CONTRAINDICATIONS

PRADAXA is contraindicated in patients with:

- Active pathological bleeding [see Warnings and Precautions (5.2) and Adverse Reactions (6.1)]
- History of a serious hypersensitivity reaction to dabigatran, dabigatran etexilate, or to one of the excipients of the product (e.g., anaphylactic reaction or anaphylactic shock) [see Adverse Reactions (6.1)]
- Mechanical prosthetic heart valve [see Warnings and Precautions (5.4)]

5 WARNINGS AND PRECAUTIONS

5.1 Increased Risk of Thrombotic Events after Premature Discontinuation

Premature discontinuation of any oral anticoagulant, including PRADAXA, in the absence of adequate alternative anticoagulation increases the risk of thrombotic events. If PRADAXA Oral Pellets are discontinued for a reason other than pathological bleeding or completion of a course of therapy, consider coverage with another anticoagulant and restart PRADAXA Oral Pellets as soon as medically appropriate [see Dosage and Administration (2.5, 2.6, 2.7)].

5.2 Risk of Bleeding

PRADAXA increases the risk of bleeding and can cause significant and, sometimes, fatal bleeding. Promptly evaluate any signs or symptoms of blood loss (e.g., a drop in hemoglobin and/or hematocrit or hypotension). Discontinue PRADAXA Oral Pellets in patients with active pathological bleeding [see Dosage and Administration (2.2)].

Risk factors for bleeding include the concomitant use of other drugs that increase the risk of bleeding (e.g., anti-platelet agents, heparin, fibrinolytic therapy, and chronic use of NSAIDs). PRADAXA's anticoagulant activity and half-life are increased in patients with renal impairment [see Clinical Pharmacology (12.2)].

Reversal of Anticoagulant Effect

Hemodialysis can remove dabigatran; however the clinical experience supporting the use of hemodialysis as a treatment for bleeding is limited [see Overdosage (10)]. Prothrombin complex concentrates or recombinant Factor VIIa may be considered but their use has not been evaluated in clinical trials. Protamine sulfate and vitamin K are not expected to affect the anticoagulant activity of dabigatran. Consider administration of platelet concentrates in cases where thrombocytopenia is present or long-acting antiplatelet drugs have been used.

In adults, a specific reversal agent (idarucizumab) for PRADAXA is available when reversal of the anticoagulant effect of dabigatran is needed. In pediatric patients, the efficacy and safety of idarucizumab have not been established.

5.3 Spinal/Epidural Anesthesia or Puncture

When neuraxial anesthesia (spinal/epidural anesthesia) or spinal puncture is employed, patients treated with anticoagulant agents are at risk of developing an epidural or spinal hematoma which can result in long-term or permanent paralysis [see Boxed Warning].

To reduce the potential risk of bleeding associated with the concurrent use of PRADAXA and epidural or spinal anesthesia/analgesia or spinal puncture, consider the pharmacokinetic profile of dabigatran [see Clinical Pharmacology (12.3)]. Placement or removal of an epidural catheter or lumbar puncture is best performed when the anticoagulant effect of dabigatran is low; however, the exact timing to reach a sufficiently low anticoagulant effect in each patient is not known.

Should the physician decide to administer anticoagulation in the context of epidural or spinal anesthesia/analgesia or lumbar puncture, monitor frequently to detect any signs or symptoms of neurological impairment, such as midline back pain, sensory and motor deficits (numbness, tingling, or weakness in lower limbs), and bowel and/or bladder dysfunction. Instruct patients to immediately report if they experience any of the above signs or symptoms. If signs or symptoms of spinal hematoma are suspected, initiate urgent diagnosis and treatment including consideration for spinal cord decompression even though such treatment may not prevent or reverse neurological sequelae.

5.4 Thromboembolic and Bleeding Events in Patients with Prosthetic Heart Valves

The safety and efficacy of PRADAXA Capsules in adult patients with bileaflet mechanical prosthetic heart valves was evaluated in the RE-ALIGN trial, in which patients with bileaflet mechanical prosthetic heart valves (recently implanted or implanted more than three months prior to enrollment) were randomized to dose-adjusted warfarin or 150 mg, 220 mg, or 300 mg of PRADAXA Capsules twice a day. RE-ALIGN was terminated early due to the occurrence of significantly more thromboembolic events (valve thrombosis, stroke, transient ischemic attack, and myocardial infarction) and an excess of major bleeding (predominantly postoperative pericardial effusions requiring intervention for hemodynamic compromise) in the PRADAXA treatment arm as compared to the warfarin treatment arm. These bleeding and thromboembolic events were seen both in patients who were initiated on PRADAXA Capsules postoperatively within three days of mechanical bileaflet valve implantation, as well as in patients whose valves had been implanted more than three months prior to enrollment. Therefore, the use of PRADAXA is contraindicated in all patients with mechanical prosthetic valves [see Contraindications (4)].

The use of PRADAXA for the prophylaxis of thromboembolic events in patients with atrial fibrillation in the setting of other forms of valvular heart disease, including the presence of a bioprosthetic heart valve, has not been studied and is not recommended.

5.5 Effect of P-gp Inducers and Inhibitors on Dabigatran Exposure

The concomitant use of PRADAXA with P-gp inducers (e.g., rifampin) reduces exposure to dabigatran and should generally be avoided [see Clinical Pharmacology (12.3)].

P-gp inhibition and impaired renal function are the major independent factors that result in increased exposure to dabigatran [see Clinical Pharmacology (12.3)]. Concomitant use of P-gp inhibitors in patients with renal impairment is expected to produce increased exposure of dabigatran compared to that seen with either factor alone.

The concomitant use of PRADAXA Oral Pellets with P-gp-inhibitors has not been studied in pediatric patients but may increase exposure to dabigatran.

5.6 Increased Risk of Thrombosis in Patients with Triple-Positive Antiphospholipid Syndrome

Direct-acting oral anticoagulants (DOACs), including PRADAXA, are not recommended for use in patients with triple-positive antiphospholipid syndrome (APS). For patients with APS (especially those who are triple-positive [positive for lupus anticoagulant, anticardiolipin, and anti-beta 2-glycoprotein I antibodies]), treatment with DOACs has been associated with increased rates of recurrent thrombotic events compared with vitamin K antagonist therapy.

6 ADVERSE REACTIONS

The following clinically significant adverse reactions are described elsewhere in the labeling:

- Increased Risk of Thrombotic Events after Premature Discontinuation [see Warnings and Precautions (5.1)]
- Risk of Bleeding [see Warnings and Precautions (5.2)]
- Spinal/Epidural Anesthesia or Puncture [see Warnings and Precautions (5.3)]
- Thromboembolic and Bleeding Events in Patients with Prosthetic Heart Valves [see Warnings and Precautions (5.4)]
- Increased Risk of Thrombosis in Patients with Triple-Positive Antiphospholipid Syndrome [see Warnings and Precautions (5.6)]

The most serious adverse reactions reported with PRADAXA were related to bleeding [see Warnings and Precautions (5.2)].

6.1 Clinical Trials Experience

Because clinical trials are conducted under widely varying conditions, adverse reactions rates observed in the clinical trials of a drug cannot be directly compared to rates in the clinical trials of another drug and may not reflect the rates observed in practice.

Pediatric Trials

Treatment of VTE in Pediatric Patients

The safety of PRADAXA in the treatment of VTE in pediatric patients was studied in one phase III trial (DIVERSITY). The DIVERSITY study was a randomized, open-label, active-controlled, parallel-group trial comparing PRADAXA with standard of care – SOC (vitamin K antagonists, low molecular weight heparin, or fondaparinux). There were 266 pediatric patients who received study treatment, 176 patients treated with PRADAXA and 90 patients treated with SOC. Patients on PRADAXA received age- and weight-adjusted dosages of an age-appropriate formulation of PRADAXA (capsules, pellets, or oral solution) twice daily.

Patients had a median age of 14 years (range: 0-17 years), 92% were white, and half the patients were male (50%). Following at least 5 days of parenteral anticoagulant therapy, the median duration of treatment with PRADAXA was 85 days (range: 1-105). Patients with estimated glomerular filtration rate (eGFR) < 50 mL/min/1.73 m^2 were excluded from the trial.

Bleeding

Data on adjudicated major bleeding, clinically relevant non-major (CRNM) bleeding, and minor bleeding events for the PRADAXA group and the SOC group in the DIVERSITY study are reported in Table 3. There was no statistically significant difference in the time to first major bleeding event.

Table 3 Summary of All Adjudicated Bleeding Events During On-Treatment Period in DIVERSITY
 | PRADAXA N (%) | Standard of Care (SOC) N (%)
Patients | N=176 | N=90
Major bleeding event^1 | 4 (2.3) | 2 (2.2)
Fatal bleeding | 0 | 1 (1.1)
Clinically relevant non-major bleeding | 2 (1.1) | 1 (1.1)
Minor bleeding | 33 (19) | 21 (23)
Major and clinically relevant non-major bleeding | 6 (3.4) | 3 (3.3)
Any bleeding | 38 (22) | 22 (24)
^1 Major bleeding event if at least one of the following criteria applied: fatal bleeding, symptomatic bleeding in a critical area or organ (intraocular, intracranial, intraspinal or intramuscular with compartment syndrome, retroperitoneal bleeding, intra-articular bleeding, or pericardial bleeding), bleeding causing a fall in hemoglobin level of 2.0 g/dL (1.24 mmol/L) or more, or leading to transfusion of 2 or more units of whole blood or red cells.

Site-specific bleeding rates were comparable between the two arms, with the exception of the rate of any gastrointestinal bleeds (5.7% in PRADAXA arm vs 1.8% in SOC arm).

Gastrointestinal Adverse Reactions

The incidence of gastrointestinal adverse reactions for patients on PRADAXA and SOC was 32% and 12%, respectively, with the following occurring in ≥ 5% of patients taking PRADAXA: dyspepsia (including term gastro-esophageal reflux disease, gastric pH decreased and esophagitis) in 9% (vs 2%), upper abdominal pain in 5% (vs 1%), vomiting in 8% (vs 2%), nausea 5% (vs 4%), and diarrhea 5% (vs 1%).

Reduction in Risk of Recurrence of VTE in Pediatric Patients

The safety of PRADAXA in the reduction in the risk of recurrence of VTE in pediatric patients was studied in one open-label single-arm trial (Study 2). Study 2 enrolled patients who required further anticoagulation due to the presence of a clinical risk factor after completing the initial treatment for confirmed VTE (for at least 3 months) or after completing the DIVERSITY study and received PRADAXA until the clinical risk factor resolved, or up to a maximum of 12 months. There were 213 pediatric patients treated with PRADAXA, in a similar fashion as in the DIVERSITY trial.

Patients had a median age of 14 years (range: 0-18 years), 91% were white, and 55% of patients were male. Patients previously enrolled on DIVERSITY accounted for 43% of patients enrolled on Study 2 (29% from PRADAXA arm and 14% from SOC arm). The median duration of treatment with PRADAXA in Study 2 was 42 weeks (range: 0-56 weeks), with 45% of patients completing the 12-month planned duration, 17% stopping due to resolution of VTE risk factors, 12% stopping due to failure to attain target dabigatran concentration and 6% had an adverse event leading to discontinuation.

During the on-treatment period of Study 2, 3 patients (1.4%) had a major bleeding event, 3 patients (1.4%) had a clinically relevant non-major bleeding event, and 44 patients (20%) had a minor bleeding event. The most common drug-related adverse reactions were dyspepsia (5%), epistaxis (3.3%), nausea (3.3%) and menorrhagia (2.8%).

The adverse reaction profile in pediatric patients was generally consistent with that of adult patients.

Hypersensitivity Reactions in Adult PRADAXA Trials

In adult DVT/PE pivotal studies, drug hypersensitivity (including urticaria, rash, and pruritus), allergic edema, anaphylactic reaction, and anaphylactic shock were reported in 0.1% of patients receiving PRADAXA Capsules.

6.2 Postmarketing Experience

The following adverse reactions have been identified during post approval use of PRADAXA. Because these reactions are reported voluntarily from a population of uncertain size, it is not always possible to reliably estimate their frequency or establish a causal relationship to drug exposure.

Blood and Lymphatic System Disorders: Agranulocytosis, neutropenia, thrombocytopenia
Gastrointestinal Disorders: Esophageal ulcer
Immune System Disorders: Angioedema
Renal and Urinary Disorders: Anticoagulant-related nephropathy
Skin and Subcutaneous Tissue Disorders: Alopecia

7 DRUG INTERACTIONS

The concomitant use of PRADAXA with P-gp inhibitors has not been studied in pediatric patients but may increase exposure to dabigatran [see Warnings and Precautions (5.5)].

8 USE IN SPECIFIC POPULATIONS

8.1 Pregnancy

Risk Summary

The limited available data on PRADAXA use in pregnant women are insufficient to determine drug-associated risks for adverse developmental outcomes. There are risks to the mother associated with untreated venous thromboembolism in pregnancy and a risk of hemorrhage in the mother and fetus associated with the use of anticoagulants (see Clinical Considerations). In pregnant rats treated from implantation until weaning, dabigatran increased the number of dead offspring and caused excess vaginal/uterine bleeding close to parturition at an exposure 2.6 times the human exposure. At a similar exposure, dabigatran decreased the number of implantations when rats were treated prior to mating and up to implantation (gestation Day 6). Dabigatran administered to pregnant rats and rabbits during organogenesis up to exposures 8 and 13 times the human exposure, respectively, did not induce major malformations. However, the incidence of delayed or irregular ossification of fetal skull bones and vertebrae was increased in the rat (see Data).

The estimated background risk of major birth defects and miscarriage for the indicated population is unknown. All pregnancies have a background risk of birth defect, loss, or other adverse outcomes. In the U.S. general population, the estimated background risk of major birth defects and miscarriage in clinically recognized pregnancies is 2-4% and 15-20%, respectively.

Clinical Considerations

Disease-associated maternal and/or embryo/fetal risk

Pregnancy confers an increased risk for thromboembolism that is higher for women with underlying thromboembolic disease and certain high-risk pregnancy conditions. Published data describe that women with a previous history of venous thrombosis are at high risk for recurrence during pregnancy.

Fetal/Neonatal adverse reaction

Use of anticoagulants, including PRADAXA, may increase the risk of bleeding in the fetus and neonate. Monitor neonates for bleeding [see Warnings and Precautions (5.2)].

Labor or delivery

All patients receiving anticoagulants, including pregnant women, are at risk for bleeding. PRADAXA use during labor or delivery in women who are receiving neuraxial anesthesia may result in epidural or spinal hematomas. Consider discontinuation or use of shorter acting anticoagulant as delivery approaches [see Warnings and Precautions (5.2, 5.3)].

Data

Animal Data

Dabigatran has been shown to decrease the number of implantations when male and female rats were treated at a dosage of 70 mg/kg (about 2.6 to 3.0 times the human exposure at MRHD of 300 mg/day based on area under the curve [AUC] comparisons) prior to mating and up to implantation (gestation Day 6). Treatment of pregnant rats after implantation with dabigatran at the same dose increased the number of dead offspring and caused excess vaginal/uterine bleeding close to parturition. Dabigatran administered to pregnant rats and rabbits during organogenesis up to maternally toxic doses of 200 mg/kg (8 and 13 times the human exposure, respectively, at a MRHD of 300 mg/day based on AUC comparisons) did not induce major malformations, but increased the incidence of delayed or irregular ossification of fetal skull bones and vertebrae in the rat.

Death of offspring and mother rats during labor in association with uterine bleeding occurred during treatment of pregnant rats from implantation (gestation Day 7) to weaning (lactation Day 21) with dabigatran at a dose of 70 mg/kg (about 2.6 times the human exposure at MRHD of 300 mg/day based on AUC comparisons).

8.2 Lactation

Risk Summary

There are insufficient data to assess the presence of dabigatran in human milk. There are no data on the effects of dabigatran on the breastfed child or on milk production. Dabigatran and/or its metabolites were present in rat milk. Breastfeeding is not recommended during treatment with PRADAXA.

8.3 Females and Males of Reproductive Potential

The risk of clinically significant uterine bleeding, potentially requiring gynecological surgical interventions, identified with oral anticoagulants including PRADAXA should be assessed in females of reproductive potential and those with abnormal uterine bleeding.

8.4 Pediatric Use

The safety and effectiveness of PRADAXA Oral Pellets for the treatment and the reduction in risk of recurrence of venous thromboembolism have been established in pediatric patients less than 12 years of age. Use of PRADAXA Oral Pellets for this indication is supported by evidence from adequate and well-controlled studies in pediatric patients. These studies included an open-label, randomized, parallel-group study and an open-label, single-arm safety study [see Adverse Reactions (6.1) and Clinical Studies (14.1, 14.2)]. Other age-appropriate pediatric formulations of dabigatran etexilate are available for pediatric patients aged 12 years and older for these indications.

Safety and effectiveness of PRADAXA have not been established in pediatric patients with non-valvular atrial fibrillation or those who have undergone hip replacement surgery.

8.5 Geriatric Use

Clinical studies of PRADAXA Oral Pellets did not include patients 65 years of age and older. Information on the use of PRADAXA Capsules in geriatric patients is available in that prescribing information.

8.6 Renal Impairment

PRADAXA has not been studied in pediatric patients with an eGFR < 50 mL/min/1.73 m^2. Reduced renal function could increase exposure. Dosing recommendations cannot be provided for treatment of these patients. Avoid use of PRADAXA in these patients [see Dosage and Administration (2.3)].

10 OVERDOSAGE

Accidental overdose may lead to hemorrhagic complications. In the event of hemorrhagic complications, initiate appropriate clinical support, discontinue treatment with PRADAXA, and investigate the source of bleeding. A specific reversal agent (idarucizumab) is available for adult patients.

Dabigatran is primarily eliminated by the kidneys with a low plasma protein binding of approximately 35%. Hemodialysis can remove dabigatran; however, data supporting this approach are limited. Using a high-flux dialyzer, blood flow rate of 200 mL/min, and dialysate flow rate of 700 mL/min, approximately 49% of total dabigatran can be cleared from plasma over 4 hours. At the same dialysate flow rate, approximately 57% can be cleared using a dialyzer blood flow rate of 300 mL/min, with no appreciable increase in clearance observed at higher blood flow rates. Upon cessation of hemodialysis, a redistribution effect of approximately 7% to 15% is seen. The effect of dialysis on dabigatran's plasma concentration would be expected to vary based on patient specific characteristics. Measurement of aPTT or ECT may help guide therapy [see Warnings and Precautions (5.2) and Clinical Pharmacology (12.2)].

11 DESCRIPTION

PRADAXA Oral Pellets contain dabigatran etexilate mesylate, a direct thrombin inhibitor. The chemical name of dabigatran etexilate mesylate is β-Alanine, N-[[2-[[[4-[[[(hexyloxy)carbonyl]amino]iminomethyl] phenyl]amino]methyl]-1-methyl-1H-benzimidazol-5-yl]carbonyl]-N-2-pyridinyl-,ethyl ester, methanesulfonate and it has a molecular formula of C34H41N7O5 ∙ CH4O3S and molecular weight of 723.86 for the mesylate salt and 627.75 for the free base. The structural formula is:

Dabigatran etexilate mesylate is a yellow-white to yellow powder. It is freely soluble in methanol, slightly soluble in ethanol, and sparingly soluble in isopropanol. A saturated solution in pure water has a solubility of 1.8 mg/mL.

Each packet of PRADAXA Oral Pellets contains 20 mg, 30 mg, 40 mg, 50 mg, 110 mg, or 150 mg dabigatran etexilate (equivalent to 23.06 mg, 34.59 mg, 46.12 mg, 57.65 mg, 126.83 mg, or 172.95 mg dabigatran etexilate mesylate) along with the following inactive ingredients: acacia, dimethicone, hydroxypropyl cellulose, hypromellose, talc, and tartaric acid.

12 CLINICAL PHARMACOLOGY

12.1 Mechanism of Action

Dabigatran and its acyl glucuronides are competitive, direct thrombin inhibitors. Because thrombin (serine protease) enables the conversion of fibrinogen into fibrin during the coagulation cascade, its inhibition prevents the development of a thrombus. Both free and clot-bound thrombin, and thrombin-induced platelet aggregation are inhibited by the active moieties.

12.2 Pharmacodynamics

At recommended therapeutic doses, dabigatran etexilate prolongs the coagulation markers such as aPTT, ECT, TT, and dTT. INR is relatively insensitive to the exposure to dabigatran and cannot be interpreted the same way as used for warfarin monitoring.

As in adults, there is a correlation between plasma dabigatran concentrations and the degree of its anticoagulant effect in pediatric patients with venous thromboembolism. The parameters dTT and ECT increased in direct linear proportion to the plasma concentration of dabigatran, whereas aPTT prolongation increases in a nonlinear fashion with dabigatran plasma concentrations.

Similar PK/PD relationships for aPTT, ECT and dTT were observed across age groups of pediatric patients (ages 26 days to < 18 years) and between pediatric and adult patients with venous thromboembolism. This similarity in PK/PD relationship suggests that similar exposure-response relationship is expected for dabigatran etexilate treatment across the pediatric age groups and adult patients.

Cardiac Electrophysiology

No prolongation of the QTc interval was observed with dabigatran etexilate at doses up to 600 mg.

12.3 Pharmacokinetics

Dabigatran etexilate mesylate is absorbed as the dabigatran etexilate ester. The ester is then hydrolyzed, forming dabigatran, the active moiety. Dabigatran is metabolized to four different acyl glucuronides and both the glucuronides and dabigatran have similar pharmacological activity. Pharmacokinetics described here refer to the sum of dabigatran and its glucuronides. Dabigatran displays dose-proportional pharmacokinetics in healthy adult subjects and adult patients in the range of doses from 10 mg to 400 mg. Given twice daily, dabigatran's accumulation factor in pediatric patients receiving pellets is 1.5-1.7.

Absorption

The absolute bioavailability of dabigatran following oral administration of dabigatran etexilate is approximately 3% to 7%. Dabigatran etexilate is a substrate of the efflux transporter P-gp. After oral administration of dabigatran etexilate in healthy volunteers, Cmax occurs at 1 hour post-administration in the fasted state. Coadministration of PRADAXA with a high-fat meal delays the time to Cmax by approximately 2 hours but has no effect on the bioavailability of dabigatran; PRADAXA may be administered with or without food.

PRADAXA is available in Capsules and Oral Pellets. The approved indications and intended age groups are not the same. Oral absorption of dabigatran etexilate is formulation-dependent. Dabigatran etexilate oral pellets show 37% higher relative bioavailability in healthy adults compared to dabigatran etexilate capsules. In addition, the relative bioavailability between the two dosage forms is age dependent. The relative bioavailability observed in adult patients cannot be translated to pediatric patients.

Distribution

Dabigatran is approximately 35% bound to human plasma proteins. The red blood cell to plasma partitioning of dabigatran measured as total radioactivity is less than 0.3. The volume of distribution of dabigatran is 50 to 70 L.

Elimination

Dabigatran is eliminated primarily in the urine. Renal clearance of dabigatran is 80% of total clearance after intravenous administration. After oral administration of radiolabeled dabigatran, 7% of radioactivity is recovered in urine and 86% in feces. The elimination half-life of dabigatran in pediatric patients receiving pellets is approximately 9 to 11 hours.

Metabolism

After oral administration, dabigatran etexilate is converted to dabigatran. The cleavage of the dabigatran etexilate by esterase-catalyzed hydrolysis to the active principal dabigatran is the predominant metabolic reaction. Dabigatran is not a substrate, inhibitor, or inducer of CYP450 enzymes. Dabigatran is subject to conjugation, forming pharmacologically active acyl glucuronides. Four positional isomers, 1-O, 2-O, 3-O, and 4-O-acylglucuronide exist, and each accounts for less than 10% of total dabigatran in plasma.

Specific Populations

Pediatric Patients

The pharmacokinetics of dabigatran was characterized in two clinical studies (DIVERSITY and Study 2) following multiple doses in pediatric patients from birth to less than 18 years old. In pediatric patients taking age- and weight-adjusted dosages of PRADAXA Oral Pellets (less than 12 years of age), the observed geometric mean steady-state trough concentration was 54.7 ng/mL (25.9 to 88.3 ng/mL, 10th to 90th percentile) compared to the geometric mean steady-state trough concentration of 59.7 ng/mL (26.3 to 146 ng/mL, 10th to 90th percentile) observed in adult patients with DVT/PE taking PRADAXA Capsules.

Renal Impairment

An open, parallel-group, single-center study compared dabigatran pharmacokinetics in healthy adult subjects and adult patients with mild to moderate renal impairment receiving a single dose of PRADAXA Capsules 150 mg. Exposure to dabigatran increases with severity of renal function impairment (Table 4). Similar findings were observed in the RE-LY, RE-COVER and RE-NOVATE II trials.

Table 4 Impact of Renal Impairment on Dabigatran Pharmacokinetics
Renal Function | CrCl (mL/min) | Increase in AUC | Increase in Cmax | t1/2 (h)
Normal | ≥ 80 | 1× | 1× | 13
Mild | 50-80 | 1.5× | 1.1× | 15
Moderate | 30-50 | 3.2× | 1.7× | 18
Severe^+ | 15-30 | 6.3× | 2.1× | 27
^+Patients with severe renal impairment were not studied in RE-LY, RE-COVER and RE-NOVATE II.

Hepatic Impairment

Administration of PRADAXA Capsules in adult patients with moderate hepatic impairment (Child-Pugh B) showed a large inter-subject variability, but no evidence of a consistent change in exposure or pharmacodynamics.

Drug Interactions

No clinical drug interaction studies have been conducted in pediatric subjects. A summary of the effect of coadministered drugs on dabigatran exposure in adult subjects is shown in Figures 1 and 2.

Figure 1 Effect of P-gp Inhibitor or Inducer (rifampicin) Drugs on Peak and Total Exposure to Dabigatran (Cmax and AUC). Shown are the Geometric Mean Ratios (Ratio) and 90% Confidence Interval (90% CI). The Perpetrator and Dabigatran Etexilate Dosage and Dosage Frequency are given as well as the Time of Perpetrator Dosage in Relation to Dabigatran Etexilate Dosage (Time Difference)

Figure 2 Effect of Non-P-gp Inhibitor or Inducer, Other Drugs, on Peak and Total Exposure to Dabigatran (Cmax and AUC). Shown are the Geometric Mean Ratios (Ratio) and 90% Confidence Interval (90% CI). The Perpetrator and Dabigatran Etexilate Dosage and Dosage Frequency are given as well as the Time of Perpetrator Dosage in Relation to Dabigatran Etexilate Dosage (Time Difference)

Impact of Dabigatran on Other Drugs

In clinical studies exploring CYP3A4, CYP2C9, P-gp, and other pathways, dabigatran did not meaningfully alter the pharmacokinetics of amiodarone, atorvastatin, clarithromycin, diclofenac, clopidogrel, digoxin, pantoprazole, or ranitidine.

13 NONCLINICAL TOXICOLOGY

13.1 Carcinogenesis, Mutagenesis, Impairment of Fertility

Dabigatran was not carcinogenic when administered by oral gavage to mice and rats for up to 2 years. The highest doses tested (200 mg/kg/day) in mice and rats were approximately 3.6 and 6 times, respectively, the human exposure at MRHD of 300 mg/day based on AUC comparisons.

Dabigatran was not mutagenic in in vitro tests, including bacterial reversion tests, mouse lymphoma assay and chromosomal aberration assay in human lymphocytes, and the in vivo micronucleus assay in rats.

In the rat fertility study with oral gavage doses of 15, 70, and 200 mg/kg, males were treated for 29 days prior to mating, during mating up to scheduled termination, and females were treated 15 days prior to mating through gestation Day 6. No adverse effects on male or female fertility were observed at 200 mg/kg or 9 to 12 times the human exposure at MRHD of 300 mg/day based on AUC comparisons. However, the number of implantations decreased in females receiving 70 mg/kg, or 3 times the human exposure at MRHD based on AUC comparisons.

14 CLINICAL STUDIES

14.1 Treatment of VTE in Pediatric Patients

The DIVERSITY study was conducted to demonstrate the efficacy and safety of PRADAXA compared to standard of care (SOC) for the treatment of venous thromboembolism (VTE) in pediatric patients from birth to less than 18 years of age. The study was designed as an open-label, randomized, parallel-group, non-inferiority study. Patients enrolled were randomized according to a 2:1 scheme to either an age-appropriate formulation (capsules, oral pellets, or oral solution) of PRADAXA (dosages adjusted for age and weight) after at least 5 days and no longer than 21 days of treatment with a parenteral anticoagulant, or to SOC comprised of low molecular weight heparins (LMWH) or vitamin K antagonists (VKA) or fondaparinux. For patients on PRADAXA, drug concentration was determined prior to the 7th dose and a single titration was permitted to achieve drug target levels of 50-250 ng/ml. Inability to achieve target, after one up-titration, resulted in premature termination of study drug in 12 patients (6.8%).

The median treatment duration during the treatment period was 85 days. In total, 267 patients entered the study (leading index VTE was 64% deep vein thrombosis, 10% cerebral venous thrombosis or sinus thrombosis, and 9.0% pulmonary embolism), with 18% of patients having a central line-associated thrombosis. The patient population was 49.8% male, 91.8% white, 4.9% Asian, and 1.5% black; 168 patients were 12 to < 18 years old, 64 patients 2 to < 12 years, and 35 patients were younger than 2 years. The concomitant VTE-related risk factors of patients in this trial among study arms were as follows: inherited thrombophilia disorder (PRADAXA: 20%; SOC: 22%), congenital heart disease (PRADAXA: 12%; SOC: 30%), heart failure (PRADAXA: 3%; SOC: 18%), history of cancer (PRADAXA: 10%; SOC: 1%), CVL insertion (PRADAXA: 23%; SOC: 27%), immobility (PRADAXA: 13%; SOC: 10%) and significant infection (PRADAXA: 15%; SOC: 13%). The number of patients taking concomitant medications with hemostatic effects was similar in both treatment groups (PRADAXA: 15%; SOC: 16%).

The efficacy of PRADAXA was established based on a composite endpoint of patients with complete thrombus resolution, freedom from recurrent venous thromboembolic event, and freedom from mortality related to venous thromboembolic event (composite primary endpoint). Of the 267 randomized patients, 81 patients (45.8%) in the dabigatran etexilate group and 38 patients (42.2%) in the SOC group met the criteria for the composite primary endpoint. The corresponding rate difference and 95% CI was -0.038 (-0.161, 0.086) and thus demonstrated non-inferiority of PRADAXA to SOC, since the upper bound of the 95% CI was lower than the predefined non-inferiority margin of 20% (see Table 5).

Table 5 Efficacy Results [ITT population] DIVERSITY Study
 | PRADAXA |  | Standard of Care
Number of patients randomized (%) | 177 (100.0) |  | 90 (100.0)
Complete thrombus resolution | 81 | (45.8) | 38 | (42.2)
Freedom from recurrent VTE | 170 | (96.0) | 83 | (92.2)
Freedom from mortality related to VTE | 177 | (100.0) | 89 | (98.9)
Composite endpoint met | 81 | (45.8) | 38 | (42.2)
Difference in rate (95% CI)^1 | -0.038 (-0.161, 0.086)
p-value for non-inferiority | < 0.0001
p-value for superiority | 0.2739
^1 Mantel-Haenszel weighted difference with age group as stratification factor

Subgroup analyses showed that there were no outliers in the treatment effect for the subgroups by age, sex, region, and presence of certain risk factors (central venous line, congenital heart disease, malignant disease). For the 3 different age strata, the proportions of patients that met the efficacy endpoint in the PRADAXA and SOC groups, respectively, were 13/22 (59.1%) and 7/13 (53.8%) for patients from birth to < 2 years [Rate Difference -0.052; (95%CI: -0.393, 0.288)], 21/43 (48.8%) and 12/21 (57.1%) for patients aged 2 to < 12 years [Rate Difference 0.083; (95%CI: -0.176, 0.342)], and 47/112 (42.0%) and 19/56 (33.9%) for patients aged 12 to < 18 years [Rate Difference -0.080; (95%CI: -0.234, 0.074)].

14.2 Reduction in the Risk of Recurrence of VTE in Pediatric Patients

Study 2 was an open-label, single-arm safety study to assess the safety of PRADAXA for the prevention of recurrent VTE in pediatric patients from birth to < 18 years. Patients who required further anticoagulation due to the presence of a clinical risk factor after completing the initial treatment for confirmed VTE (for at least 3 months) or after completing the DIVERSITY study were included in the study. Eligible patients received age- and weight-adjusted dosages of an age-appropriate formulation (capsules or oral pellets) of PRADAXA until the clinical risk factor resolved, or up to a maximum of 12 months. The primary endpoints of the study included the recurrence of VTE, major and minor bleeding events, and mortality (overall and related to thrombotic or thromboembolic events) at 6 and 12 months.

Of the 214 patients in the study, 162 patients were 12 to < 18 years old, 43 patients were 2 to < 12 years old, and 9 patients were aged 6 months to < 2 years old.

The overall probability of being free from recurrence of VTE during the on-treatment period was 0.990 (95% CI: 0.960, 0.997) at 3 months, 0.984 (95% CI: 0.950, 0.995) at 6 months, and 0.984 (95% CI: 0.950, 0.995) at 12 months. The probability of being free from bleeding events during the on-treatment period was 0.849 (95% CI: 0.792, 0.891) at 3 months, 0.785 (95% CI: 0.718, 0.838) at 6 months, and 0.723 (95% CI: 0.645, 0.787) at 12 months. No on-treatment deaths occurred.

16 HOW SUPPLIED/STORAGE AND HANDLING

PRADAXA Oral Pellets are yellowish in a silver-colored, child-resistant packet. The packets are placed in an aluminum bag with a desiccant. PRADAXA Oral Pellets are supplied as follows:

Strength | Package | NDC
20 mg | unit of use carton with 1 aluminum bag containing 60 packets | 0597-0425-78
30 mg | unit of use carton with 1 aluminum bag containing 60 packets | 0597-0430-18
40 mg | unit of use carton with 1 aluminum bag containing 60 packets | 0597-0435-96
50 mg | unit of use carton with 1 aluminum bag containing 60 packets | 0597-0440-53
110 mg | unit of use carton with 1 aluminum bag containing 60 packets | 0597-0445-87
150 mg | unit of use carton with 1 aluminum bag containing 60 packets | 0597-0450-16

STORAGE AND HANDLING

Store at 20°C to 25°C (68°F to 77°F); excursions permitted to 15°C to 30°C (59°F to 86°F) [see USP Controlled Room Temperature]. Store in the original package to protect from moisture.

Do not open the packets until ready for use. Use the PRADAXA Oral Pellets within 6 months of opening the aluminum bag containing the packets.

17 PATIENT COUNSELING INFORMATION

Advise the patient or caregiver to read the FDA-approved patient labeling (Medication Guide and Instruction for Use).

Instructions for Patients

- Tell patients or their caregivers to take or administer PRADAXA Oral Pellets exactly as prescribed.
- Tell patients or their caregivers to remove desiccant from the aluminum bag and throw away.
- Remind patients or their caregivers not to discontinue PRADAXA Oral Pellets without talking to the healthcare provider who prescribed it.
- Provide the following instructions on administration to the patients or caregivers:
  - Take the prescribed dosage of PRADAXA Oral Pellets twice a day, approximately 12 hours apart;
  - PRADAXA Oral Pellets may be sprinkled on mashed carrots, apple sauce, or mashed banana, or may be taken with approximately 1-2 ounces of apple juice;
  - PRADAXA Oral Pellets should not be mixed with milk or with foods that contain milk;
  - Once the PRADAXA Oral Pellets are mixed with the soft food or apple juice, the patient should take the dose within 30 minutes;
  - If a dose of PRADAXA Oral Pellets is not taken at the scheduled time, the dose should be skipped if it cannot be taken at least 6 hours before the next scheduled dose. The dose of PRADAXA Oral Pellets should not be doubled to make up for a missed dose.

[see Boxed Warning, and Dosage and Administration (2.2, 2.4)]

Bleeding

Inform patients or their caregivers that they may bleed more easily, may bleed longer, and should call their healthcare provider for any signs or symptoms of bleeding [see Warnings and Precautions (5.2)].

Instruct patients or their caregivers to seek emergency care right away if they have any of the following, which may be a sign or symptom of serious bleeding:

- Unusual bruising (bruises that appear without known cause or that get bigger)
- Pink or brown urine
- Red or black, tarry stools
- Coughing up blood
- Vomiting blood, or vomit that looks like coffee grounds

Instruct patients or their caregivers to call their healthcare provider or to get prompt medical attention if they experience any signs or symptoms of bleeding:

- Pain, swelling or discomfort in a joint
- Headaches, dizziness, or weakness
- Reoccurring nose bleeds
- Unusual bleeding from gums
- Bleeding from a cut that takes a long time to stop
- Menstrual bleeding or vaginal bleeding that is heavier than normal

If patients have had neuraxial anesthesia or spinal puncture, and particularly, if they are taking concomitant NSAIDs or platelet inhibitors, advise patients or their caregivers to watch for signs and symptoms of spinal or epidural hematoma, such as back pain, tingling, numbness (especially in the lower limbs), muscle weakness, and stool or urine incontinence. If any of these symptoms occur, advise the patient or their caregivers to contact his or her physician immediately [see Boxed Warning].

Gastrointestinal Adverse Reactions

Instruct patients or their caregivers to call their healthcare provider if they experience any signs or symptoms of dyspepsia or gastritis:

- Dyspepsia (upset stomach), burning, or nausea
- Abdominal pain or discomfort
- Epigastric discomfort, GERD (gastric indigestion)

[see Adverse Reactions (6.1)]

Invasive or Surgical Procedures

Instruct patients or their caregivers to inform their healthcare provider that they are taking PRADAXA before any invasive procedure (including dental procedures) is scheduled [see Dosage and Administration (2.7)].

Concomitant Medications

Ask patients or their caregivers to list all prescription medications, over-the-counter medications, or dietary supplements they are taking or plan to take so the patient's healthcare provider knows about other treatments that may affect bleeding risk (e.g., aspirin or NSAIDs) or dabigatran exposure (e.g., dronedarone or systemic ketoconazole) [see Warnings and Precautions (5.2, 5.5)].

Prosthetic Heart Valves

Instruct patients or their caregivers to inform their healthcare provider if they will have or have had surgery to place a prosthetic heart valve [see Warnings and Precautions (5.4)].

Allergic Reactions

Advise caregivers that some adults taking PRADAXA have developed symptoms of an allergic reaction. Advise caregivers to inform their child's healthcare provider if their child develops symptoms of an allergic reaction, such as hives, rash, or itching. Advise caregivers to seek emergency medical attention for their child if they develop chest pain or tightness, swelling of the face or tongue, trouble breathing or wheezing, or feeling dizzy or faint.

Pregnancy

Advise patients to inform their healthcare provider immediately if they become pregnant or intend to become pregnant during treatment with PRADAXA [see Use in Specific Populations (8.1)].

Lactation

Advise patients not to breastfeed if they are taking PRADAXA [see Use in Specific Populations (8.2)].

Distributed by:
Boehringer Ingelheim Pharmaceuticals, Inc.
Ridgefield, CT 06877 USA

PRADAXA is a registered trademark of and used under license from Boehringer Ingelheim International GmbH.

Copyright © 2025 Boehringer Ingelheim Pharmaceuticals, Inc.
ALL RIGHTS RESERVED

COL8834FF232025

SPL8854F

MEDICATION GUIDE
PRADAXA (pra dax a)
(dabigatran etexilate)
Oral Pellets

This Medication Guide is for PRADAXA Oral Pellets. If your child is over 8 years of age and your healthcare provider prescribes PRADAXA Capsules for your child, read the Medication Guide that comes with your medicine.
Read this Medication Guide before you start giving PRADAXA Oral Pellets to your child and each time you get a refill. There may be new information. This Medication Guide does not take the place of talking with your healthcare provider about your child's medical condition or their treatment.

What is the most important information I should know about PRADAXA?
Do not stop giving PRADAXA without talking to the healthcare provider who prescribes it for your child. Stopping PRADAXA increases your child's risk of a clot forming in their blood.
PRADAXA may need to be stopped, if possible, before surgery or a medical or dental procedure. Ask the healthcare provider who prescribed PRADAXA for your child when your child should stop taking it. Your healthcare provider will tell you when you may start giving PRADAXA to your child again after their surgery or procedure. If your child has to stop taking PRADAXA, your healthcare provider may prescribe another medicine to help prevent a blood clot from forming.

- PRADAXA can cause bleeding which can be serious, and sometimes lead to death. This is because PRADAXA is a blood thinner medicine that lowers the chance of blood clots forming in the body.
- Your child may have a higher risk of bleeding if your child takes PRADAXA and:
  - has kidney problems
  - has stomach or intestine bleeding that is recent or keeps coming back, or a stomach ulcer
  - takes other medicines that increase the risk of bleeding, including:
    - aspirin or aspirin-containing products
    - long-term (chronic) use of non-steroidal anti-inflammatory drugs (NSAIDs)
    - a medicine that contains warfarin sodium
    - a medicine that contains heparin
    - a medicine that contains clopidogrel bisulfate
    - a medicine that contains prasugrel
  - has certain kidney problems and also takes a medicine that contains dronedarone or ketoconazole tablets
  Tell your healthcare provider if your child takes any of these medicines. Ask your healthcare provider or pharmacist if you are not sure if your child's medicine is one listed above.
- PRADAXA can increase your child's risk of bleeding because it lessens the ability of your child's blood to clot. During treatment with PRADAXA:
  - he or she may bruise more easily
  - it may take longer for any bleeding to stop
  Call your healthcare provider or get medical help right away if your child has any of these signs or symptoms of bleeding:
  - unexpected bleeding or bleeding that lasts a long time, such as:
    - unusual bleeding from the gums
    - nose bleeds that happen often
    - menstrual bleeding or vaginal bleeding that is heavier than normal
  - bleeding that is severe or you cannot control
  - pink or brown urine
  - red or black stools (looks like tar)
  - bruises that happen without a known cause or get larger
  - cough up blood or blood clots
  - vomit blood or your vomit looks like "coffee grounds"
  - unexpected pain, swelling, or joint pain
  - headaches, feeling dizzy or weak
  Take PRADAXA Oral Pellets exactly as prescribed. Do not stop giving PRADAXA Oral Pellets to your child without first talking to the healthcare provider who prescribes it for your child. Stopping PRADAXA increases your child's risk of a clot forming in their blood.
- Spinal or epidural blood clots (hematoma). People who take a blood thinner medicine (anticoagulant) like PRADAXA, and have medicine injected into their spinal and epidural area, or have a spinal puncture have a risk of forming a blood clot that can cause long-term or permanent loss of the ability to move (paralysis). Your child's risk of developing a spinal or epidural blood clot is higher if:
  - a thin tube called an epidural catheter is placed in your child's back to give them certain medicine
  - your child takes NSAIDs or a medicine to prevent blood from clotting
  - your child has a history of difficult or repeated epidural or spinal punctures
  - your child has a history of problems with their spine or has had surgery on their spine
  If your child takes PRADAXA and receives spinal anesthesia or has a spinal puncture, your healthcare provider should watch your child closely for symptoms of spinal or epidural blood clots. Tell your healthcare provider right away if your child has back pain, tingling, numbness, muscle weakness (especially in the legs and feet), loss of control of the bowels or bladder (incontinence).

See "What are the possible side effects of PRADAXA?" for more information about side effects.

What is PRADAXA Oral Pellets?
PRADAXA Oral Pellets is a prescription medicine that is used to:

- treat blood clots in children who are age 3 months to less than 12 years of age who have received an injectable medicine to treat their blood clots for at least 5 days.
- reduce the risk of blood clots happening again in children who are age 3 months to less than 12 years of age who have already been treated for blood clots.

Do not give PRADAXA if your child:

- currently has certain types of abnormal bleeding. Talk to your healthcare provider before giving PRADAXA if your child currently has unusual bleeding.
- has had a serious allergic reaction to any of the ingredients in PRADAXA. See the end of this Medication Guide for a complete list of ingredients in PRADAXA. Ask your healthcare provider if you are not sure.
- has ever had or if there are plans for your child to have a valve in their heart replaced with a mechanical (artificial) prosthetic heart valve.

Before giving PRADAXA to your child, tell your healthcare provider about all of your child's medical conditions, including if they:

- have kidney problems
- have ever had bleeding problems
- have ever had stomach ulcers
- have antiphospholipid syndrome (APS)
- are pregnant or plan to become pregnant. It is not known if PRADAXA will harm your child's unborn baby.
  - If your child is able to become pregnant, talk with your healthcare provider about your child's risk for severe uterine bleeding during treatment with blood thinner medicines, including PRADAXA.
  - Tell your healthcare provider right away if your child becomes pregnant during treatment with PRADAXA Oral Pellets.
- are breastfeeding or plan to breastfeed. It is not known if PRADAXA passes into your child's breastmilk. Your child should not breastfeed during treatment with PRADAXA.

Tell all of your healthcare providers and dentists that your child is taking PRADAXA. They should talk to the healthcare provider who prescribed PRADAXA for your child before your child has any surgery or a medical or dental procedure.
Tell your healthcare provider about all the medicines your child takes, including prescription and over-the-counter medicines, vitamins, and herbal supplements.
Some of your child's other medicines may affect the way PRADAXA works. Certain medicines may increase your child's risk of bleeding. See "What is the most important information I should know about PRADAXA?"
Especially tell your healthcare provider if your child takes a medicine that contains rifampin.
Know the medicines your child takes. Keep a list of them and show it to your healthcare provider and pharmacist when your child gets a new medicine.

How should I give PRADAXA?

- See the detailed "Instructions for Use" that comes with PRADAXA Oral Pellets for information about the right way to prepare and give your child a dose of PRADAXA Oral Pellets.
- Your healthcare provider will decide how long your child should take PRADAXA Oral Pellets. Do not stop giving your child PRADAXA Oral Pellets without first talking with your healthcare provider. Stopping PRADAXA Oral Pellets may increase your child's risk of forming blood clots.
- Give PRADAXA Oral Pellets exactly as prescribed by your healthcare provider. Check with your healthcare provider if you are not sure.
- Your healthcare provider will prescribe the correct dose of PRADAXA Oral Pellets for your child. Your healthcare provider will change your child's dose as they grow, and as needed during treatment.
- Give PRADAXA Oral Pellets 2 times a day, 1 dose in the morning and 1 dose in the evening. The doses should be given as close as possible to every 12 hours, and at about the same time every day.
- Give PRADAXA Oral Pellets before meals to help ensure that your child takes the full dose.
- You can mix PRADAXA Oral Pellets with apple juice or the following soft foods at room temperature:

- Mashed carrots

- Apple sauce

- Mashed bananas

- Do not mix PRADAXA Oral Pellets with any food or liquid other than the ones listed above.
- Do not mix PRADAXA Oral Pellets with milk or with foods that contain milk.
- Give PRADAXA Oral Pellets right away or within 30 minutes after mixing. Do not give PRADAXA Oral Pellets if they have been in contact with the soft food or apple juice for more than 30 minutes.
- Do not give PRADAXA Oral Pellets using a syringe or through a feeding tube.
- Do not run out of PRADAXA Oral Pellets. Refill your child's prescription before you run out.
- If you plan for your child to have surgery, or a medical or a dental procedure, tell your healthcare provider and dentist that your child is taking PRADAXA Oral Pellets. Your child may have to stop taking PRADAXA Oral Pellets for a short time. See "What is the most important information I should know about PRADAXA?"
- If your child only takes part of their dose, do not give another dose at that time. Give your child their next dose at the regular scheduled time, about 12 hours later.
- If your child misses a dose of PRADAXA Oral Pellets, give it as soon as you remember. If your child's next dose is less than 6 hours away, skip the missed dose. Do not give your child a double dose of PRADAXA Oral Pellets to make up for a missed dose.
- If your child takes too much PRADAXA Oral Pellets, go to the nearest hospital emergency room or call your healthcare provider right away.
- Call your healthcare provider right away if your child falls or injures himself, especially if your child hits his head. Your healthcare provider may need to check your child.

PRADAXA Oral Pellets come in an aluminum bag that contains packets of the Oral Pellets used to prepare your child's dose of medicine. After opening the aluminum bag, the packets of PRADAXA Oral Pellets must be used within 6 months. See "How should I store PRADAXA Oral Pellets?"

What are the possible side effects of PRADAXA?
PRADAXA can cause serious side effects. See "What is the most important information I should know about PRADAXA?"

- Allergic Reactions. Some adults taking PRADAXA Capsules have developed symptoms of an allergic reaction.
  - Call your healthcare provider if your child gets symptoms of an allergic reaction, such as:

- hives

- rash

- itching

- Get medical help right away if your child gets any of the following symptoms of a serious allergic reaction with PRADAXA Oral Pellets:

- chest pain or chest tightness
- swelling of the face or tongue

- trouble breathing or wheezing
- feeling dizzy or faint

Common side effects of PRADAXA in children include:

- indigestion, upset stomach, burning
- nausea, vomiting, or diarrhea
- stomach-area (abdominal) pain or discomfort

Call your healthcare provider if your child develops any of the signs and symptoms of stomach and intestine problems listed above.
Tell your healthcare provider if your child has any side effect that bothers them or that does not go away.
These are not all of the possible side effects of PRADAXA. For more information, ask your healthcare provider or pharmacist.
Call your doctor for medical advice about side effects. You may report side effects to FDA at 1-800-FDA-1088.

How should I store PRADAXA Oral Pellets?

- Store PRADAXA Oral Pellets at room temperature 68°F to 77°F (20°C to 25°C).
- After opening the silver aluminum bag that contains the packets of Oral Pellets:
  - The silver aluminum bag contains a desiccant container. Throw away (dispose of) the desiccant container in your household trash.
  - PRADAXA Oral Pellets must be used within 6 months. Safely throw away any unused PRADAXA Oral Pellets after 6 months.
- Keep PRADAXA Oral Pellets packets in the original silver aluminum bag to keep them dry (protect the packets from moisture). Do not open packets of PRADAXA Oral Pellets until you are ready to use them.
- Throw away any PRADAXA Oral Pellets that have not been given within 30 minutes after the Oral Pellets come into contact with apple juice or soft food.

Keep PRADAXA and all medicines out of the reach of children.

General information about the safe and effective use of PRADAXA
Medicines are sometimes prescribed for purposes other than those listed in a Medication Guide. Do not use PRADAXA for a condition for which it was not prescribed. Do not give PRADAXA to other people, even if they have the same symptoms that your child has. It may harm them.
This Medication Guide summarizes the most important information about PRADAXA. If you would like more information, talk with your child's healthcare provider. You can ask your child's pharmacist or healthcare provider for information about PRADAXA that is written for health professionals.

What are the ingredients in PRADAXA Oral Pellets?
Active ingredient: dabigatran etexilate mesylate
Inactive ingredients: acacia, dimethicone, hydroxypropyl cellulose, hypromellose, talc, and tartaric acid.
Distributed by: Boehringer Ingelheim Pharmaceuticals, Inc. Ridgefield, CT 06877 USA
For more information about PRADAXA Oral Pellets, call Boehringer Ingelheim Pharmaceuticals, Inc. at 1-800-542-6257.
Copyright © 2025 Boehringer Ingelheim Pharmaceuticals, Inc.
ALL RIGHTS RESERVED
COL8834FF232025

This Medication Guide has been approved by the U.S. Food and Drug Administration.

Revised: 6/2025

Instructions for Use PRADAXA (pra dax a) (dabigatran etexilate) Oral Pellets

Read the Medication Guide and this Instructions for Use that come with PRADAXA Oral Pellets for the most important information you need to know before giving PRADAXA Oral Pellets to your child for the first time, and each time you get a refill. The information may have changed. This Instructions for Use does not take the place of talking to your healthcare provider about your child's medical condition or treatment.

Your healthcare provider should tell you the amount (dose) of PRADAXA Oral Pellets to give your child. Your child's dose of PRADAXA Oral Pellets will change as they grow.

Important Information

- PRADAXA Oral Pellets can be used in children as soon as they are able to swallow soft food
- Do not open the packets of PRADAXA Oral Pellets until you are ready to use them
- Give PRADAXA Oral Pellets either with soft foods or apple juice
- Do not give PRADAXA Oral Pellets using syringes or through feeding tubes
- Do not mix PRADAXA Oral Pellets with milk or soft foods containing milk products
- Give your child the prepared dose of PRADAXA Oral Pellets before meals to help ensure that your child takes the full dose
- Give PRADAXA Oral Pellets to your child right away or within 30 minutes after mixing
- Do not give PRADAXA Oral Pellets if they have been in contact with the food or apple juice for more than 30 minutes
- If your child does not take all of the mixed PRADAXA Oral Pellets, do not give another dose at that time. Give the next scheduled dose about 12 hours later.
- If a dose of PRADAXA Oral Pellets is not taken at the scheduled time, the dose should be taken as soon as possible on the same day; the missed dose should be skipped if it cannot be taken at least 6 hours before the next scheduled dose. The dose of PRADAXA Oral Pellets should not be doubled to make up for a missed dose.

Instructions are provided below for preparing and giving a dose of PRADAXA Oral Pellets with soft foods and preparing and giving a dose of PRADAXA Oral Pellets with apple juice.

How to prepare and give a dose of PRADAXA Oral Pellets with soft foods:

The food should be at room temperature before mixing with the pellets. Use only one of the following soft foods:

- Mashed carrots
- Apple sauce (for administration with apple juice see below)
- Mashed banana

Do not mix with milk, milk products, or soft foods containing milk products.

Step 1 – Prepare cup or bowl

- Place 2 teaspoons of the soft food into a small cup or bowl.

Step 2 – Collect PRADAXA Oral Pellets packet(s)

- Open the silver aluminum bag by cutting at the top with scissors. The aluminum bag contains 60 silver-colored packets of PRADAXA Oral Pellets and a desiccant container.
- Remove desiccant container from silver aluminum bag. Throw away (dispose of) desiccant container in your household trash.
- Do not open or eat the desiccant.

- Remove the prescribed number of PRADAXA Oral Pellets packets from the silver aluminum bag.
- Leave the unused packets of PRADAXA Oral Pellets in the silver aluminum bag.

Step 3 – Open the PRADAXA Oral Pellets packet(s)

- Tap the packet of Oral Pellets on a flat surface to ensure that the contents settle to the bottom.

- Keep the packet of Oral Pellets in an upright position and open the packet by cutting at the top with scissors.

Step 4 – Add the PRADAXA Oral Pellets to soft food

- Empty the entire packet into the small cup or bowl containing the soft food.
- Repeat Steps 3 and 4 if more than one packet is needed.
- Throw away the empty packets in your household trash.

Step 5 – Stir the soft food to mix with the PRADAXA Oral Pellets

- Stir the pellets into the soft food with a spoon to mix well.

Step 6 – Give the soft food and oral pellet mixture

- Give the soft food and oral pellet mixture to your child right away.
- Make sure that your child eats all of the soft food and oral pellet mixture.

How to prepare and give a dose of PRADAXA Oral Pellets with apple juice:

Step 1 – Pour about 1 to 2 ounces of apple juice into a clean drinking cup.
Step 2 – Collect PRADAXA Oral Pellets packet(s)

- Open the silver aluminum bag by cutting at the top with scissors. The silver aluminum bag includes 60 silver-colored packets of pellets and a desiccant container.
- Remove desiccant container from silver aluminum bag. Throw away (dispose of) desiccant container in your household trash.
- Do not open or eat the desiccant.

- Remove the prescribed number of PRADAXA Oral Pellets packets from the silver aluminum bag.
- Leave the unused packets of PRADAXA Oral Pellets in the silver aluminum bag.

Step 3 – Open PRADAXA Oral Pellets packet(s)

- Tap the packet on a flat surface to make sure that the contents settle to the bottom.

- Keep the packet in an upright position and open the packet by cutting at the top with scissors.

Step 4 – Mix the PRADAXA Oral Pellets with apple juice

- Spoon the PRADAXA Oral Pellets from the packet into your child's mouth. Offer your child as much apple juice as needed to swallow the PRADAXA Oral Pellets. Make sure all of the PRADAXA Oral Pellets are swallowed.
  OR

- Mix the PRADAXA Oral Pellets in a small amount of apple juice that your child is likely to drink completely. Make sure all of the PRADAXA Oral Pellets are swallowed. If any of the PRADAXA Oral Pellets stick to the cup, add a little more apple juice and give it to your child. Repeat until no PRADAXA Oral Pellets remain in the cup.

Storing PRADAXA Oral Pellets

- Store PRADAXA Oral Pellets at room temperature from 68°F to 77°F (20°C to 25°C).
- After opening the silver aluminum bag that contains the packets of Oral Pellets:
  - The silver aluminum bag contains a desiccant container. Throw away (dispose of) the desiccant container in your household trash.
  - PRADAXA Oral Pellets must be used within 6 months. Safely throw away any unused PRADAXA Oral Pellets after 6 months.
- Keep PRADAXA Oral Pellets packets in the original silver aluminum bag to keep them dry (protect the packets from moisture). Do not open packets of PRADAXA Oral Pellets until you are ready to use them.
- Throw away any PRADAXA Oral Pellets that have not been given within 30 minutes after the Oral Pellets come into contact with apple juice or food.

Keep PRADAXA Oral Pellets and all medicines out of the reach of children.

For more information about PRADAXA Oral Pellets, call Boehringer Ingelheim Pharmaceuticals, Inc. at 1-800-542-6257.

Distributed by: Boehringer Ingelheim Pharmaceuticals, Inc. Ridgefield, CT 06877 USA
Copyright © 2025 Boehringer Ingelheim Pharmaceuticals, Inc.
ALL RIGHTS RESERVED

COL8834FF232025

This Instructions for Use has been approved by the U.S. Food and Drug Administration.
Revised: 6/2025

PRINCIPAL DISPLAY PANEL - 20 mg Packet Bag Carton

NDC 0597-0425-78

DISPENSE IN THIS UNIT OF USE CONTAINER
WITH ENCLOSED MEDICATION GUIDE

Pradaxa®
(dabigatran etexilate)
Oral Pellets

20 mg* per packet

Pradaxa oral pellets are NOT substitutable on a mg-to-mg basis with other dabigatran
etexilate dosage forms.

Do not open PRADAXA packets until you are ready to use them. Discard unused
PRADAXA oral pellets 6 months after first opening the aluminum bag.

1 aluminum bag containing 60 packets
Rx only

Boehringer
Ingelheim

PRINCIPAL DISPLAY PANEL - 30 mg Packet Bag Carton

NDC 0597-0430-18

DISPENSE IN THIS UNIT OF USE CONTAINER
WITH ENCLOSED MEDICATION GUIDE

Pradaxa®
(dabigatran etexilate)
Oral Pellets

30 mg* per packet

Pradaxa oral pellets are NOT substitutable on a mg-to-mg basis with other dabigatran
etexilate dosage forms.

Do not open PRADAXA packets until you are ready to use them. Discard unused
PRADAXA oral pellets 6 months after first opening the aluminum bag.

1 aluminum bag containing 60 packets
Rx only

Boehringer
Ingelheim

PRINCIPAL DISPLAY PANEL - 40 mg Packet Bag Carton

NDC 0597-0435-96

DISPENSE IN THIS UNIT OF USE CONTAINER
WITH ENCLOSED MEDICATION GUIDE

Pradaxa®
(dabigatran etexilate)
Oral Pellets

40 mg* per packet

Pradaxa oral pellets are NOT substitutable on a mg-to-mg basis with other dabigatran
etexilate dosage forms.

Do not open PRADAXA packets until you are ready to use them. Discard unused
PRADAXA oral pellets 6 months after first opening the aluminum bag.

1 aluminum bag containing 60 packets
Rx only

Boehringer
Ingelheim

PRINCIPAL DISPLAY PANEL - 50 mg Packet Bag Carton

NDC 0597-0440-53

DISPENSE IN THIS UNIT OF USE CONTAINER
WITH ENCLOSED MEDICATION GUIDE

Pradaxa®
(dabigatran etexilate)
Oral Pellets

50 mg* per packet

Pradaxa oral pellets are NOT substitutable on a mg-to-mg basis with other dabigatran
etexilate dosage forms.

Do not open PRADAXA packets until you are ready to use them. Discard unused
PRADAXA oral pellets 6 months after first opening the aluminum bag.

1 aluminum bag containing 60 packets
Rx only

Boehringer
Ingelheim

PRINCIPAL DISPLAY PANEL - 110 mg Packet Bag Carton

NDC 0597-0445-87

DISPENSE IN THIS UNIT OF USE CONTAINER
WITH ENCLOSED MEDICATION GUIDE

Pradaxa®
(dabigatran etexilate)
Oral Pellets

110 mg* per packet

Pradaxa oral pellets are NOT substitutable on a mg-to-mg basis with other dabigatran
etexilate dosage forms.

Do not open PRADAXA packets until you are ready to use them. Discard unused
PRADAXA oral pellets 6 months after first opening the aluminum bag.

1 aluminum bag containing 60 packets
Rx only

Boehringer
Ingelheim

PRINCIPAL DISPLAY PANEL - 150 mg Packet Bag Carton

NDC 0597-0450-16

DISPENSE IN THIS UNIT OF USE CONTAINER
WITH ENCLOSED MEDICATION GUIDE

Pradaxa®
(dabigatran etexilate)
Oral Pellets

150 mg* per packet

Pradaxa oral pellets are NOT substitutable on a mg-to-mg basis with other dabigatran
etexilate dosage forms.

Do not open PRADAXA packets until you are ready to use them. Discard unused
PRADAXA oral pellets 6 months after first opening the aluminum bag.

1 aluminum bag containing 60 packets
Rx only

Boehringer
Ingelheim